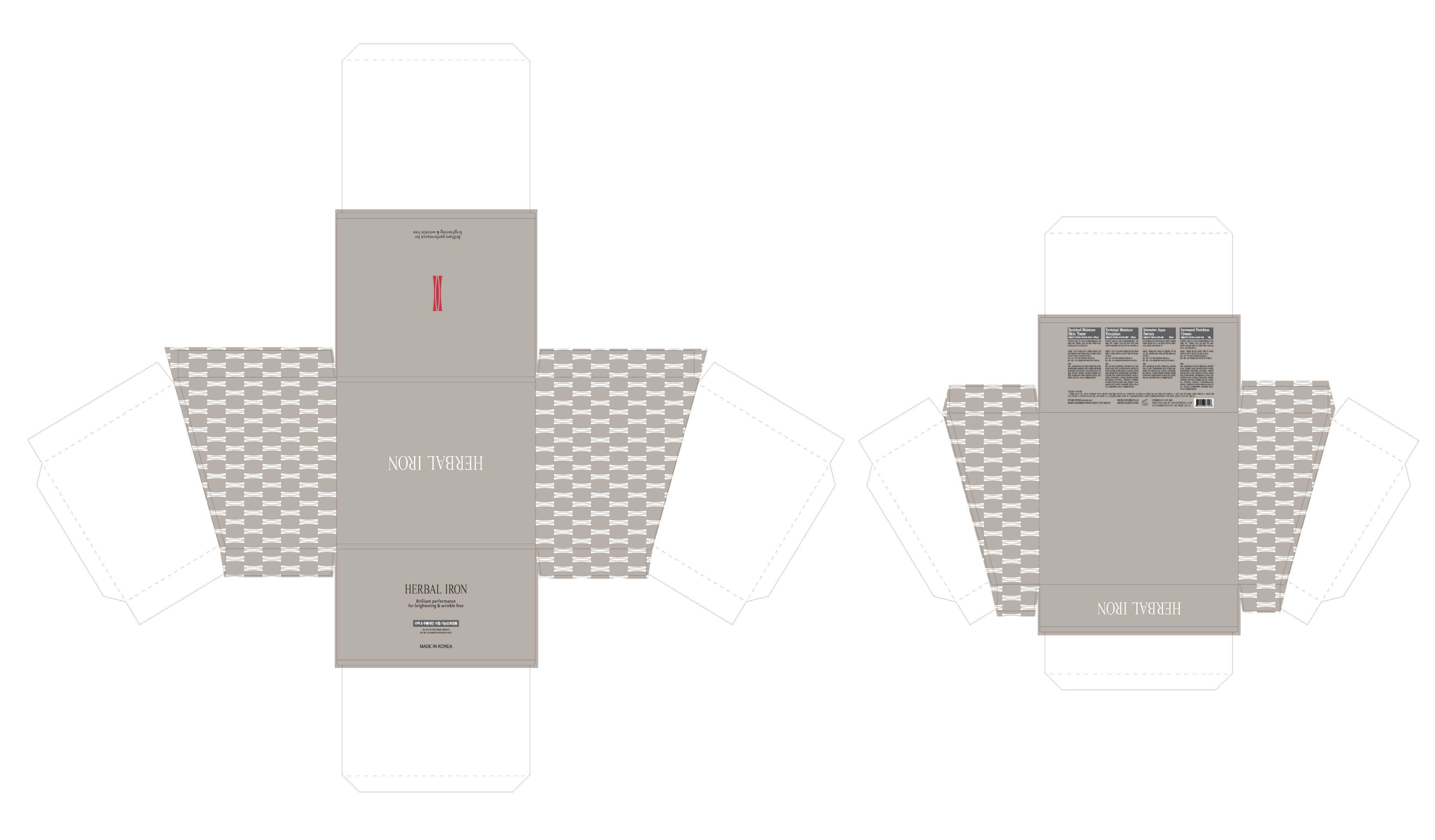 DRUG LABEL: HERBAL IRON BRILLIANT PERFORMANCE FOR BRIGHTENING AND WRINKLE FREE
NDC: 71324-0015 | Form: KIT | Route: TOPICAL
Manufacturer: BTGIN CO.,LTD
Category: otc | Type: HUMAN OTC DRUG LABEL
Date: 20170327

ACTIVE INGREDIENTS: GINSENOSIDES 0.05 g/100 mL; ADENOSINE 0.04 g/100 mL; ADENOSINE 0.04 g/100 mL; GINSENOSIDES 0.05 g/100 mL; GINSENOSIDES 0.1 g/100 mL; ADENOSINE 0.04 g/100 mL; ADENOSINE 0.04 g/100 g; GINSENOSIDES 0.1 g/100 g
INACTIVE INGREDIENTS: GLYCERIN; WATER; BUTYLENE GLYCOL; WATER; BUTYLENE GLYCOL; GLYCERIN; WATER; GLYCERIN; BUTYLENE GLYCOL; WATER; GLYCERIN; BUTYLENE GLYCOL

ACTIVE INGREDIENT

Ginsenosides, Adenosine

INACTIVE INGREDIENT

Water, Glycerin, Butylene Glycol, Etc.

PURPOSE

Skin Protectant - Brightening & Wrinkle-Free

Keep out of reach of the children

INDICATIONS AND USAGE

Apply proper amount to the skin

WARNINGS

1. Do not use in the following cases(Eczema and scalp wounds)
2.Side Effects
1)Due to the use of this druf if rash, irritation, itching and symptopms of hypersnesitivity occur dicontinue use and consult your phamacisr or doctor
3.General Precautions
1)If in contact with the eyes, wash out thoroughty with water If the symptoms are servere, seek medical advice immediately
2)This product is for exeternal use only. Do not use for internal use
4.Storage and handling precautions
1)If possible, avoid direct sunlight and store in cool and area of low humidity
2)In order to maintain the quality of the product and avoid misuse
3)Avoid placing the product near fire and store out in reach of children

DOSAGE AND ADMINISTRATION

for external use only